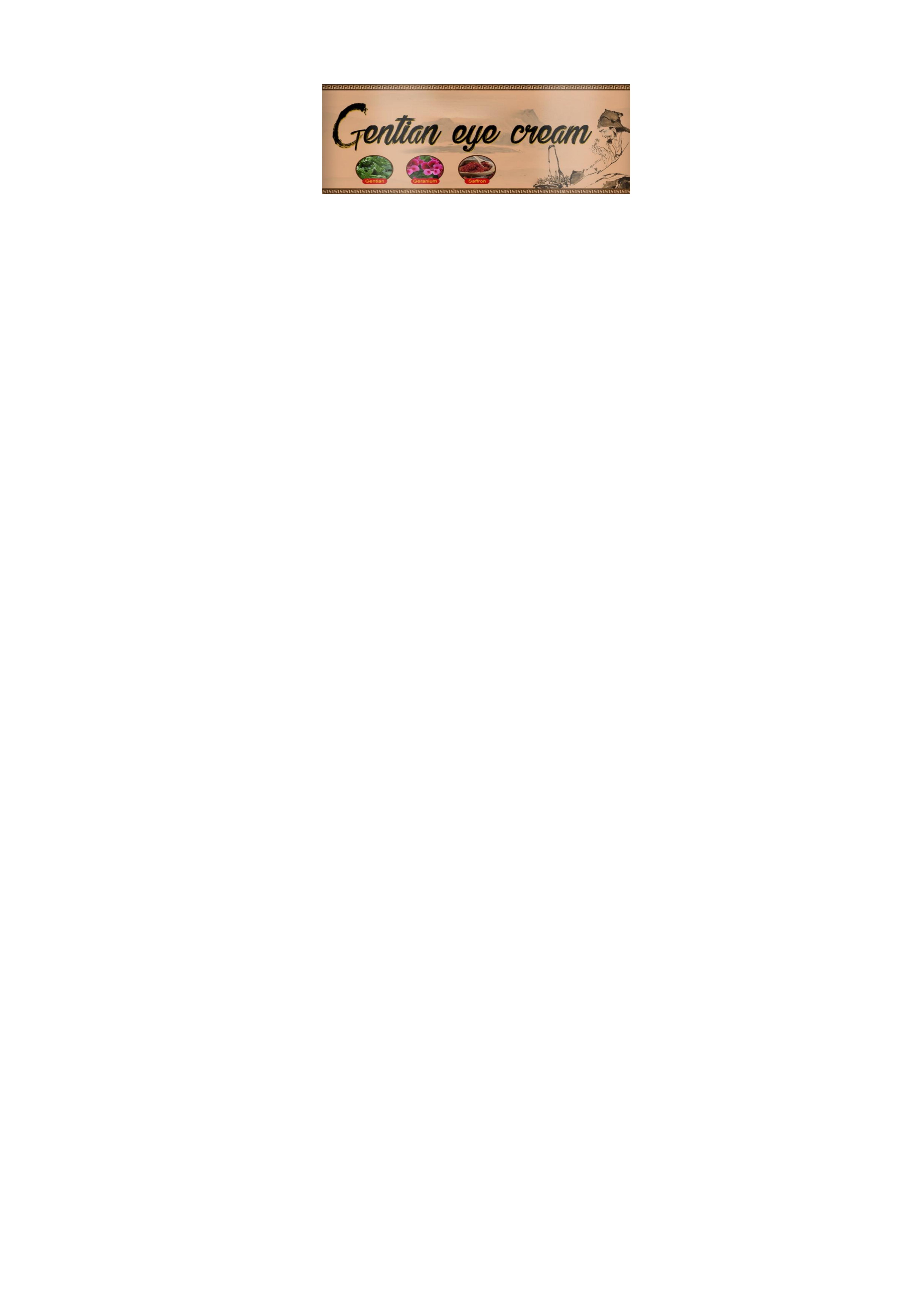 DRUG LABEL: Centian eye cream
NDC: 84864-106 | Form: CREAM
Manufacturer: Yiwu Jingmo trade Co., LTD
Category: otc | Type: HUMAN OTC DRUG LABEL
Date: 20241211

ACTIVE INGREDIENTS: COPPER TRIPEPTIDE-1 5 g/100 g
INACTIVE INGREDIENTS: GLYCERIN; PANTOTHENIC ACID; AQUA; PALMITOYL PENTAPEPTIDE-4; PALMITOYL TETRAPEPTIDE-7; PROPYLENE GLYCOL; PALMITOYL TRIPEPTIDE-1

COMPONENTS

Copper Tripeptide-1：5%

PURPOSE

Remove bags under the eyes

INDICATIONS AND USAGE

Apply to skin until absorbed

WARNINGS

Prohibit ingestion by mouth.

Do not put into eyes or ears.

No contact with wounds.

DOSAGE AND ADMINISTRATION

For external use only.

Skin irritation occurs, wash with water, discontinue use

If symptoms do not improve, seek medical attention immediately

WHEN USING

Skin irritation occurs, wash with water, discontinue use

If symptoms do not improve, seek medical attention immediately。

Allow 5 minutes for the product to take effect

STOP USE

Wound breaks

KEEP OUT OF REACH OF CHILDREN

If sxralowed, get medical help or contact a Poison Conirol Cenler ngiht away

INACTIVE INGREDIENT

Aqua，Glycerin，Propylene Glycol，Palmitoyl Tripeptide-1，Palmitoyl Tetrapeptide-7，Palmitoyl Pentapeptide-4，，Pantothenic Acid